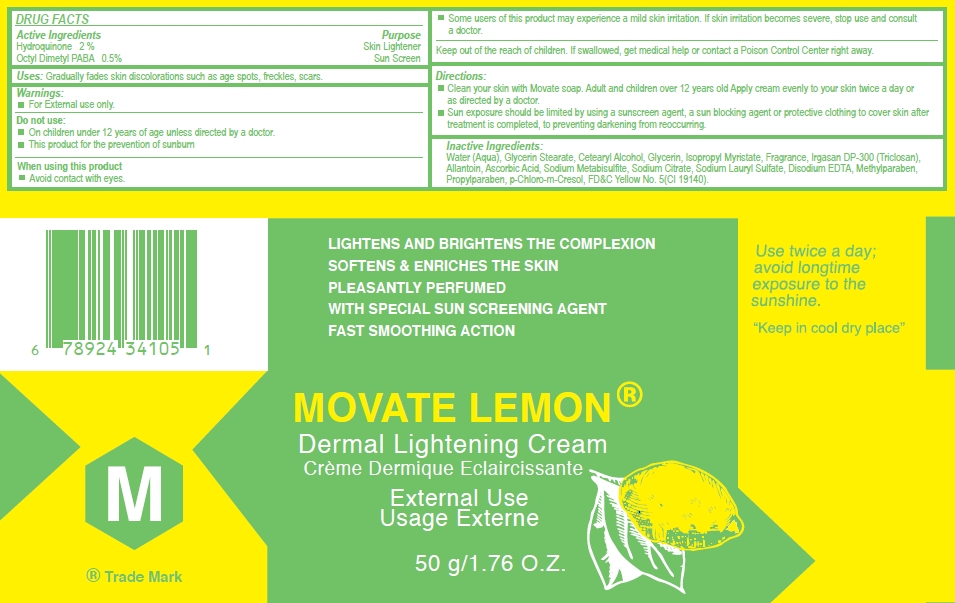 DRUG LABEL: Movate Skin Lightening Lemon
NDC: 66129-111 | Form: CREAM
Manufacturer: International Beauty Exchange
Category: otc | Type: HUMAN OTC DRUG LABEL
Date: 20110623

ACTIVE INGREDIENTS: HYDROQUINONE 1 g/50 g; PADIMATE O .25 g/50 g
INACTIVE INGREDIENTS: WATER; GLYCERYL STEARATE CITRATE; CETOSTEARYL ALCOHOL; GLYCERIN; ISOPROPYL MYRISTATE; TRICLOSAN; ALLANTOIN; ASCORBIC ACID; SODIUM METABISULFITE; SODIUM CITRATE; SODIUM LAURYL SULFATE; EDETATE DISODIUM; METHYLPARABEN; PROPYLPARABEN; CHLOROCRESOL; FD&C YELLOW NO. 5

Drug Facts

ACTIVE INGREDIENT

Hydroquinone 2%

Padimate, O 0.5%

WARNINGS

For external use only

DO NOT USE

On children under 12 years of age unless directed by a doctor

WHEN USING

Avoid contact with eyes.

INDICATIONS AND USAGE

For the gradual fading of dark (brownish) areas in the skin such as freckles, age and liver spots

PURPOSE

Skin Lightener

DOSAGE AND ADMINISTRATION

Apply a small amount as a thin layer on the affected area twice daily, or use as directed by a doctor

KEEP OUT OF REACH OF CHILDREN

If swallowed, get medical help or contact a Poison Control Center right away

INACTIVE INGREDIENT

WATER,GLYCERYL STEARATE CITRATE, CETOSTEARYL ALCOHOL, GLYCERIN, ISOPROPYL MYRISTATE,TRICLOSAN, ALLANTOIN, ASCORBIC ACID, SODIUM METABISULFITE, SODIUM LAURYL SULFATE, SODIUM CITRATE, EDETATE DISODIUM, METHYLPARABEN,